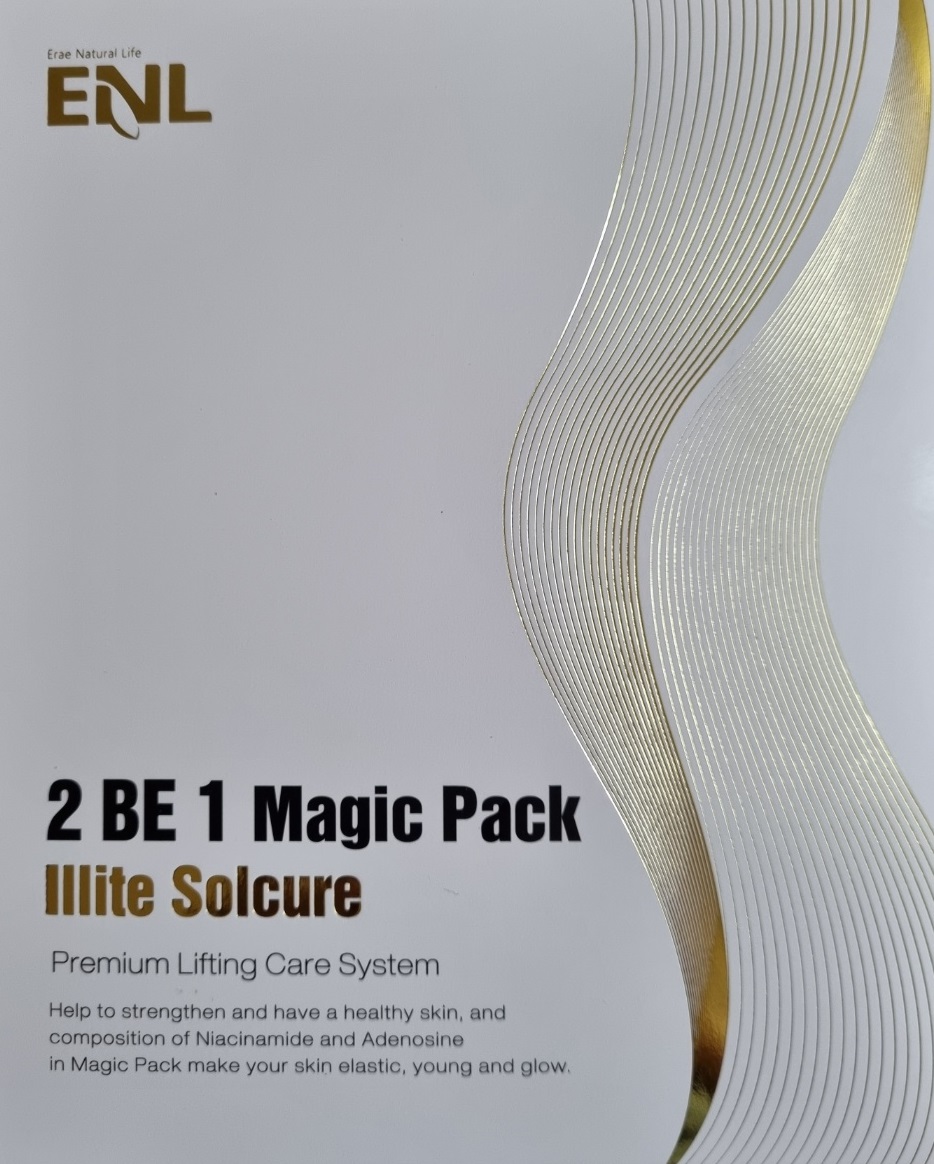 DRUG LABEL: Solcure 2 be1 Magic Pack
NDC: 83235-0005 | Form: LIQUID
Manufacturer: Erae Natural Life
Category: otc | Type: HUMAN OTC DRUG LABEL
Date: 20230202

ACTIVE INGREDIENTS: ADENOSINE 0.08 g/100 g; NIACINAMIDE 4 g/100 g
INACTIVE INGREDIENTS: WATER; GLYCERIN

Drug Facts

ACTIVE INGREDIENT

niacinamide, adenosine

INACTIVE INGREDIENT

(1)

Water
Glycerin
Dipropylene Glycol
Chamaecyparis Obtusa Water
illite
Algin
Sodium Polyacrylate
Vincetoxicum Atratum Extract
Butylene Glycol
Ectoin
Fucus Vesiculosus Extract
Prunella Vulgaris Extract
Allantoin
Dipotassium Glycyrrhizate
C13-14 Isoalkane
Laureth-7
1,2-Hexanediol
Caprylyl Glycol
Fragrance

(2)

Water
Chamaecyparis Obtusa Water
Glycerin
Dipropylene Glycol
Calcium chloride
Butylene Glycol
Vincetoxicum Atratum Extract
Illite Extract
Fucus Vesiculosus Extract
Prunella Vulgaris Extract
Allantoin
Dipotassium Glycyrrhizate
1,2-Hexanediol
Caprylyl Glycol
Fragrance

PURPOSE

whitening, wrinkle care

keep out or reach of the children

INDICATIONS AND USAGE

(1) Apply an appropriate amount to the face,

(2) Apply this product on the skin, remove the support after 10-20 minutes, and apply the remaining product evenly.

WARNINGS

This product is for exeternal use only. Do not use for internal use
Storage and handling precautions
If possible, avoid direct sunlight and store in cool and area of low humidity in order to maintain the quality of the product and avoid misuse
Avoid placing the product near fire and store out in reach of children

- consult a physician in case of abnormal symptoms, such as red spots, swelling or itching, or side effects in the areas of application due to direct light during or after using the product

- do not use on wounded area

DOSAGE AND ADMINISTRATION

for external use only